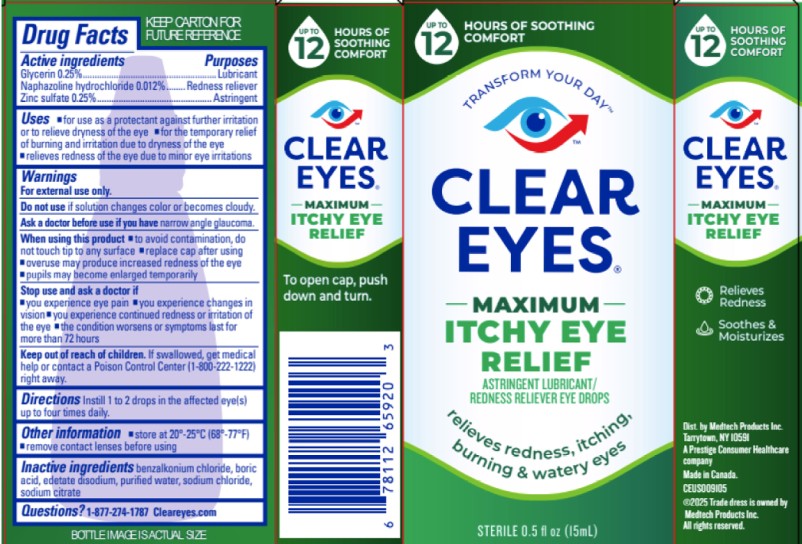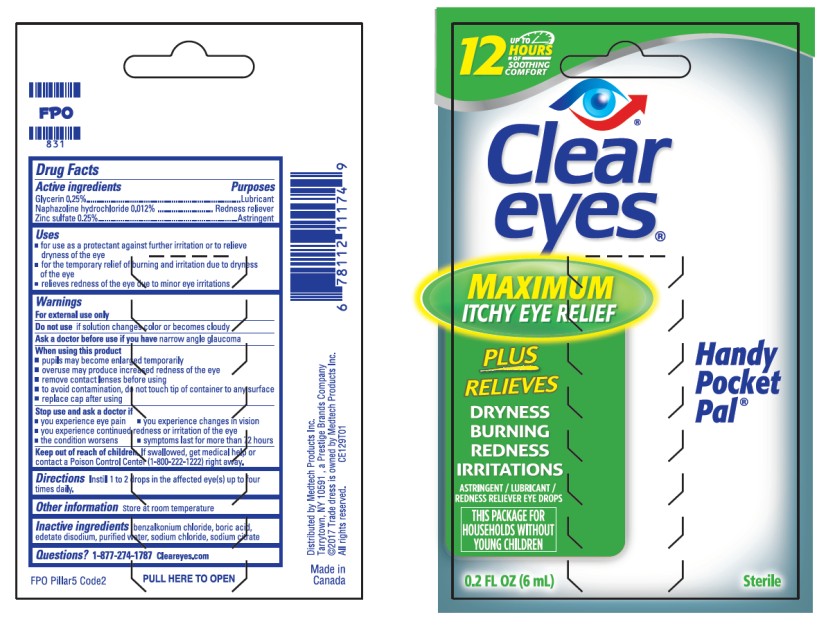 DRUG LABEL: Clear Eyes Maximum Itchy Eye Relief
NDC: 67172-999 | Form: LIQUID
Manufacturer: Prestige Brands Holdings, Inc.
Category: otc | Type: HUMAN OTC DRUG LABEL
Date: 20251023

ACTIVE INGREDIENTS: GLYCERIN 2.5 mg/1 mL; NAPHAZOLINE HYDROCHLORIDE .12 mg/1 mL; ZINC SULFATE 2.5 mg/1 mL
INACTIVE INGREDIENTS: BENZALKONIUM CHLORIDE; BORIC ACID; EDETATE DISODIUM; WATER; SODIUM CHLORIDE; SODIUM CITRATE

Clear Eyes Maximum Itchy Eye Relief

Drug Facts

Active Ingredient

Glycerin 0.25%

Purpose

Lubricant

Active Ingredient

Naphazoline hydrochloride 0.012%

Purpose

Redness Reliever

Active Ingredient

Zinc Sulfate 0.25%

Purpose

Astringent

Uses

- for use as a protectant against further irritation or to relieve dryness of the eye
- for the temporary relief of burning & irritation due to dryness of the eye
- relieves redness of the eye due to minor eye irritations

Warnings

For external use only

Do not use if

solution changes color or becomes cloudy

Ask a doctor before use if you have

narrow angle glaucoma

When using this product

- to avoid contamination, do not touch tip to any surface
- replace cap after using
- overuse may produce increased redness of the eye
- overuse may produce increased redness of the eye

Stop use and ask a doctor if

- you experience eye pain
- you experience changes in vision
- you experience continued redness or irritation of the eye
- the condition worsens or symptoms last for more than 72 hours

Keep out of reach of children.

If swallowed, get medical help or contact a Poison Control Center (1-800-222-1222) right away.

Directions

Instill 1 to 2 drops in the affected eye(s) up to four times daily.

Other Information

- Store at 20-25C (68-77F)
- remove contact lenses before using

Inactive Ingredients

benzalkonium chloride, boric acid, edetate disodium, purified water, sodium chloride, sodium citrate

Questions?

1-877-274-1787 Cleareyes.com

PRINCIPAL DISPLAY PANEL

CLEAR
EYES®
MAXIMUM
ITCHY EYE

RELIEF
ASTRINGENT LUBRICANT/
REDNESS RELIEVER EYE DROPS